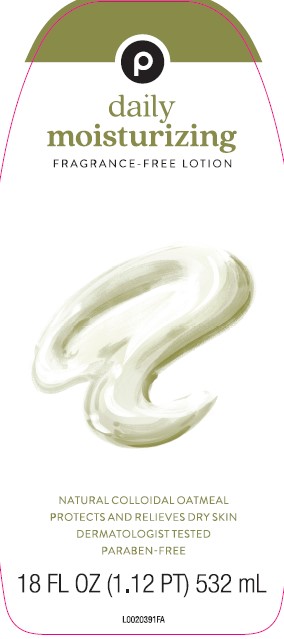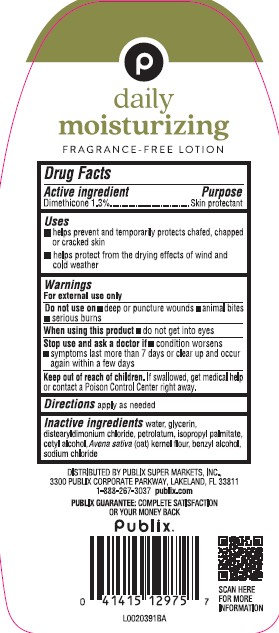 DRUG LABEL: Daily Moisturizing
NDC: 56062-619 | Form: LOTION
Manufacturer: Publix Super Markets, Inc.
Category: otc | Type: HUMAN OTC DRUG LABEL
Date: 20260205

ACTIVE INGREDIENTS: DIMETHICONE 13 mg/1 mL
INACTIVE INGREDIENTS: WATER; GLYCERIN; DISTEARYLDIMONIUM CHLORIDE; PETROLATUM; ISOPROPYL PALMITATE; CETYL ALCOHOL; OATMEAL; BENZYL ALCOHOL; SODIUM CHLORIDE

Publix 619.003/619AC rev 2
Daily Moisturizing Lotion

Claims

P

daily moisturizing

FRAGRANCE-FREE LOTION

Active ingredient

Dimethicone 1.3%

Purpose

Skin protectant

Uses

- helps prevent and temporarily protects chafed, chapped or cracked skin
- helps protect from the drying effects of wind and cold weather

Warnings

For external use only

Do not use on

- deep or puncture wounds
- animal bites
- serious burns

When using this product

- do not get into eyes

Stop use and ask a doctor if

- condition worsens
- symptoms last more than 7 days or cleat up and occur again within a few days

Keep out of reach of children.

If swallowed, get medical help or contact a Poison Control Center right away.

Directions

apply as needed

Inactive ingredients

water, glycerin, distearyldimonium chloride, petrolatum, isopropyl palmitate, cetyl alcohol, Avena sativa (oat) kernel flour, benzyl alcohol, sodium chloride

Adverse Reaction

Distributed by Publix Super Markets, Inc

3300 Publix Corporate Parkway, Lakeland, FL 33811

1-888-267-3037 publix.com

PUBLIX GUARANTEE: COMPLETE SATISFACTION OR YOUR MONEY BACK

Publix®

SCAN HERE FOR MORE INFORMATION

principal display panel

P

daily moisturizing

FRAGRANCE-FREE LOTION

NATURAL COLLOIDAL OATMEAL

PROTECTS AND RELIEVES DRY SKIN

DERMATOLOGIST TESTED

PARABEN-FREE

18 FL OZ (1.12 PT) 532 mL